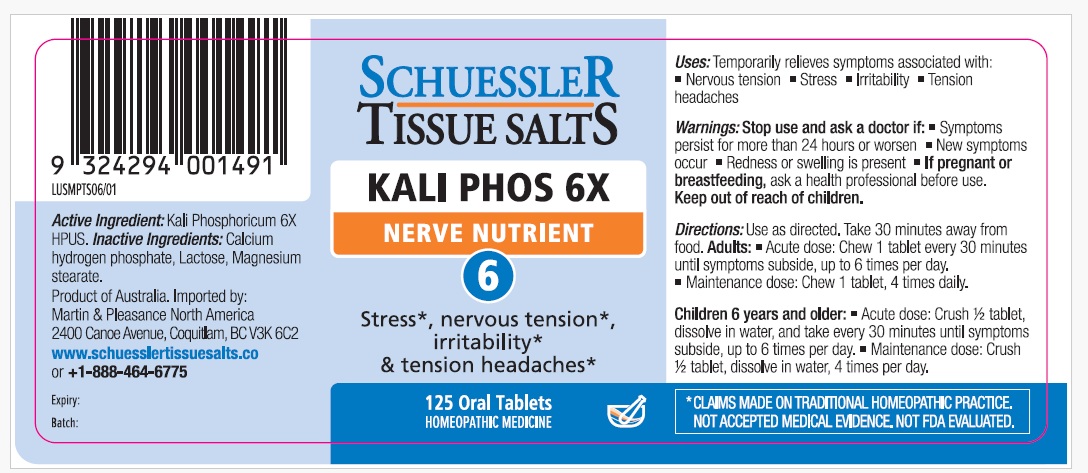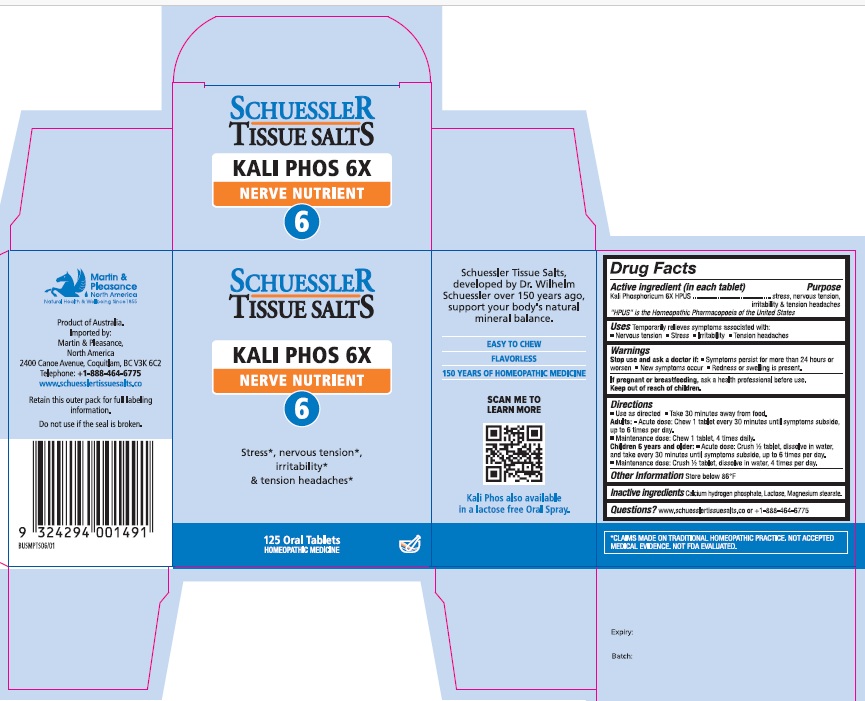 DRUG LABEL: Schuessler Tissue Salts Kali Phos Nerve Nutrient 6
NDC: 84999-018 | Form: TABLET, CHEWABLE
Manufacturer: Martin & Pleasance Pty Ltd
Category: homeopathic | Type: HUMAN OTC DRUG LABEL
Date: 20250718

ACTIVE INGREDIENTS: DIBASIC POTASSIUM PHOSPHATE 6 [hp_X]/1 1
INACTIVE INGREDIENTS: MAGNESIUM STEARATE; LACTOSE MONOHYDRATE; ANHYDROUS DIBASIC CALCIUM PHOSPHATE

Active Ingredients Purpose

Kali Phosphoricum 6X HPUS stress, nervous tension, irritability and tension headaches

" HPUS" is the Homeopathic Pharmacopoeia of the United States

Uses

Temporarily relieves symptoms associated with

- Nervous tension
- Stress
- Irritability
- Tension headaches

Warnings

Stop use and ask a doctor if

- Symptoms persist for more than 24 hours or worsen
- New symptoms occur
- Redness or swelling is present.

If pregnant or breastfeeding, ask a health professional before use. Keep out of reach of children.

Directions

- Use as directed
- Take 30 minutes away from food

Adults: Acute dose: Chew 1 tablet every 30 minutes until symptoms subside up to 6 times per day.

Maintenance dose: Chew 1 tablet, 4 times daily.

Children 6 years and older: Acute dose: Crush 1/2 tablet, dissolve in water, and take every 30 minutes until symptoms subside, up to six times per day.

Maintenance dose :Crush 1/2 tablet, dissolve in water, 4 times per day.

Other Information

Store below 86°F

Inactive Ingredients

Calcium hydrogen phosphate, Lactose, Magnesium stearate

Questions?www.schuesslertissuesalts.co or + 1-888-464-6775